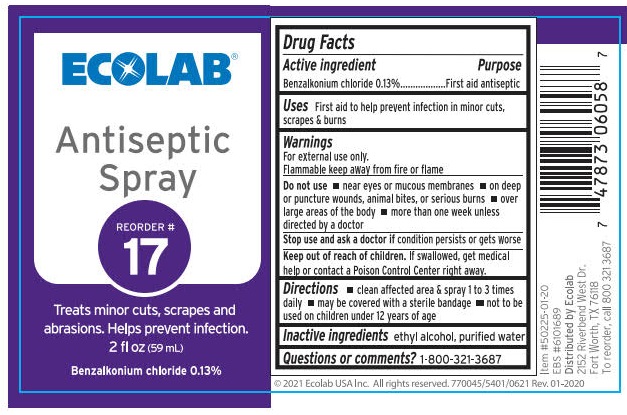 DRUG LABEL: ECOLAB Antiseptic
NDC: 71338-122 | Form: SPRAY
Manufacturer: ECOLAB Food Safety and Specialties, Inc.
Category: otc | Type: HUMAN OTC DRUG LABEL
Date: 20250909

ACTIVE INGREDIENTS: BENZALKONIUM CHLORIDE 1.3 g/1 L
INACTIVE INGREDIENTS: ALCOHOL; WATER

ECOLAB Antiseptic Spray

Drug Facts

Active ingredient

Benzalkonium Chloride 0.13%

Purpose

First aid antiseptic

Uses

First aid to help prevent infections & for temporary pain relief of minor cuts, scrapes & burns.

Warnings

For external use only.

Flammable, keepaway from fire or flame.

Do not use

- near eyes or mucus membranes
- on deep or puncture wounds, animal bites, or serious burns
- over large areas of the body
- for more than one week unless directed by a doctor

Stop use and ask a doctor if condition persisits or gets worse

Keep out of reach of children. If swallowed, get medical help or contact a Poison Control Center right away.

Directions

- clean affected area & spray 1 to 3 times daily
- may be covered with a sterile bandage
- not to be used on children under 12 years of age

Inactive ingredients ethyl alcohol, purified water

Questions or comments?

1-800-321-3687

PACKAGE LABEL

ECOLAB®

Antiseptic Spray

Reorder

# 17

Treats minor cuts, scrapes and abrasions. Helps Prevent infection.

2 fl oz (59 mL)

Benzalkonium chloride 0.13%